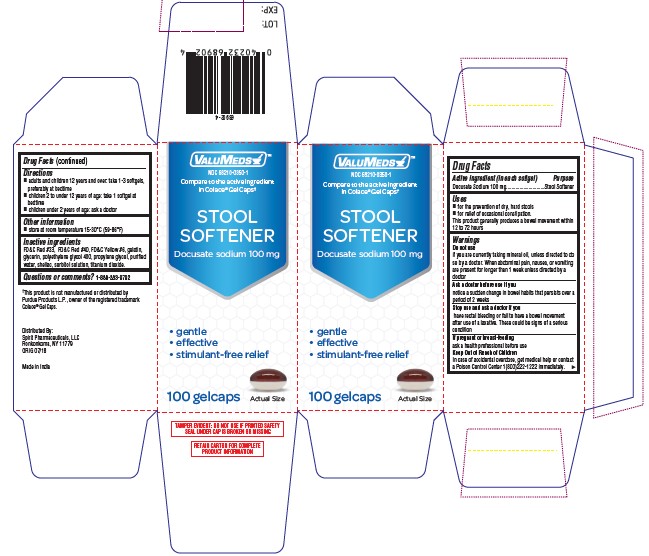 DRUG LABEL: DOCUSATE SODIUM
NDC: 68210-0350 | Form: CAPSULE, LIQUID FILLED
Manufacturer: Spirit Pharmaceuticals LLC
Category: otc | Type: HUMAN OTC DRUG LABEL
Date: 20241213

ACTIVE INGREDIENTS: DOCUSATE SODIUM 100 mg/1 1
INACTIVE INGREDIENTS: POLYETHYLENE GLYCOL 400; PROPYLENE GLYCOL; SHELLAC; WATER; GELATIN; GLYCERIN; SORBITOL; D&C RED NO. 33; FD&C RED NO. 40; FD&C YELLOW NO. 6; TITANIUM DIOXIDE

STOOL SOFTENER

Drug Facts

Active ingredient (in each gelcaps)

Docusate Sodium 100 mg

Purpose

Stool Softner

Uses

- for the prevention of the dry, hard stools
- for relief of occassional constipation. This product generally produces a bowel movement within 12 to 72 hours

Do not use

if you are currently taking mineral oil, unless directed to so by a doctor.

When abdominal pain, nausea, or vomiting are present for longer than 1 week unless directed by a doctor

Ask a doctor before use if you

notice a sudden change in bowel habits that persists over a period of 2 weeks

Stop use abd ask a doctor if you

have rectal bleeding fail to have a bowel movement occur after use.

If pregnant or breast-feeding

ask a health professional before use

Keep out of reach of children

In case of accidental overdose, get medical help or contact a Poison Control Center 1(800)222-1222 immediately.

Stop use and ask a doctor if you

have rectal bleeding fail to have bowel movement occur after use.

If pregnant or breast feeding

Ask a health professional before use

Keep out of reach of children

In case of accidental overdose, get medical help or contact a Poison Control Center 1-800-222-1222 immediately.

Directions

- adult and children 12 years and over: take 1-3 gelcaps, preferably at bedtime

- children 2 to under 12 years of age: take 1 gelcap at bedtime
- children under 2 years of age: ask a doctor

Other information

- Store at room temperature 15-30°C (59-86°F)
- do not use if safety seal under cap is torn or missing

Inactive ingredients

FD&C Red #33, FD&C Red#40, FD&C Yellow#6, gelatin,

glycerin, polyethylene glycol 400, propylene glycol, purified

water, shellac, sorbitol solution, titanium dioxide.

Questions or comments?

1-888-333-9792

PRICNIPAL DISPLAY PANEL

Compare to the active ingredient in

Colace ® Gel Caps *

STOOL

SOFTENER

DOCUSATE SODIUM 100 mg

Gentle
Effective
Stimulant-Free Relief
100 GELCAPS